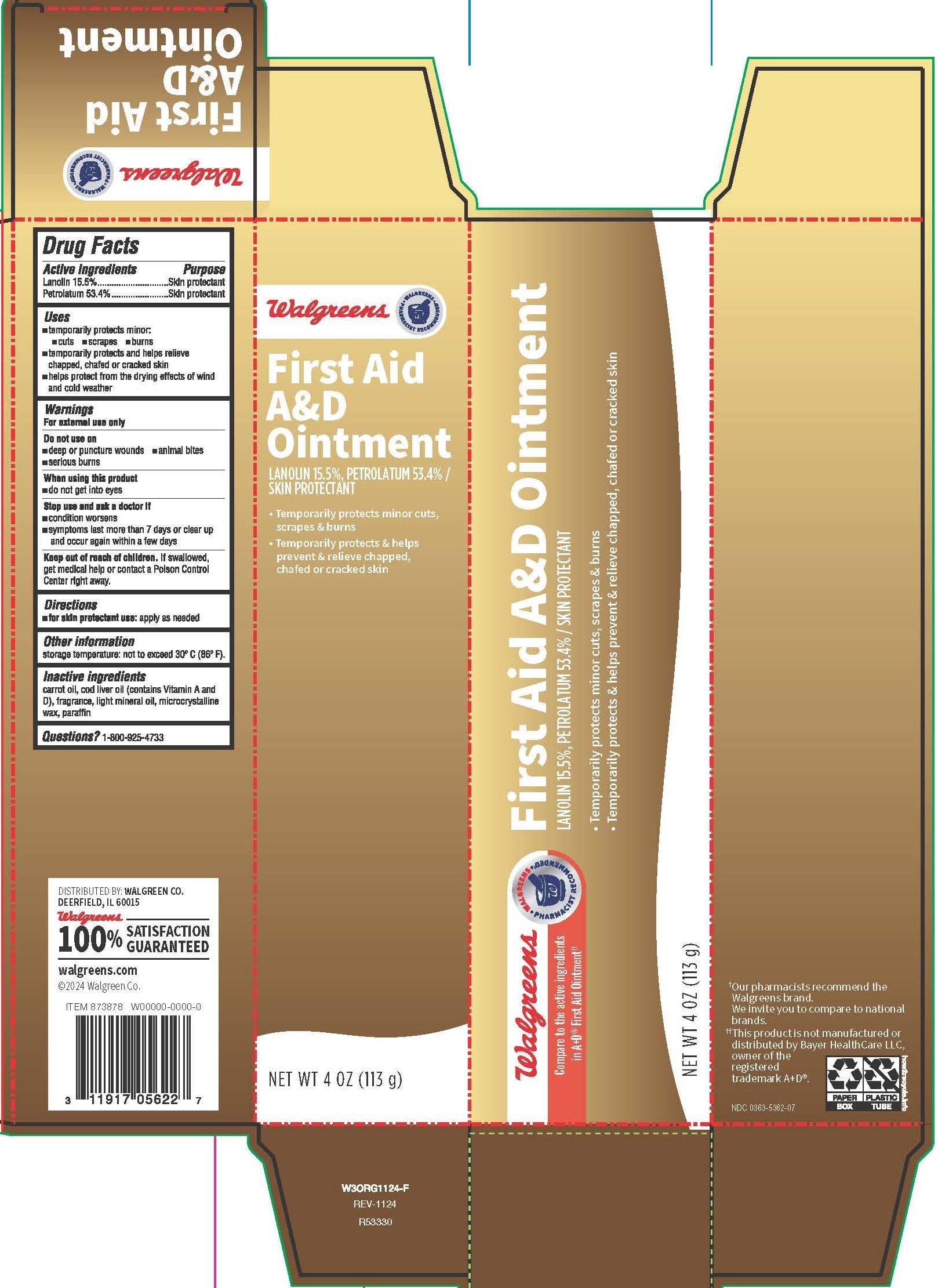 DRUG LABEL: First Aid A and D
NDC: 0363-5362 | Form: OINTMENT
Manufacturer: Walgreen Company
Category: otc | Type: HUMAN OTC DRUG LABEL
Date: 20251031

ACTIVE INGREDIENTS: LANOLIN 15.5 g/100 g; PETROLATUM 53.4 g/100 g
INACTIVE INGREDIENTS: MICROCRYSTALLINE WAX; CARROT SEED OIL; LIGHT MINERAL OIL; COD LIVER OIL; PARAFFIN

6253 First Aid-Walgreen

Drug Facts

Active ingredients

Lanolin 15.5%

Petrolatum 53.4%

Purpose

Skin protectant

Skin protectant

Uses

- temporarily protects minor:
- cuts
- scrapes
- burns
- temporarily protects and helps relieve chapped, chafed or cracked skin
- helps protect from the drying effects of wind and cold weather

Warnings

For external use only

Do not use on

- deep or puncture wounds
- animal bites
- serious burns

When using this product

- do not get into eyes

Stop use and ask a doctor if

- condition worsens
- symptoms last more than 7 days or clear up and occur again within a few days

Keep out of reach of children.

OVERDOSAGE

If swallowed, get medical help or contact a Poison Control Center right away.

Directions

- for skin protectant use: apply as needed

Other information

storage temperature: not to exceed 30° C (86° F).

Inactive ingredients

carrot oil, cod liver oil (contains Vitamin A and D), fragrance, light mineral oil, microcrystalline wax, paraffin

Questions?

1-800-925-4733

DISTRIBUTED BY: WALGREEN CO.

DEERFIELD, IL 60015

Walgreens 100% SATISFACTION GUARANTEED

walgreens.com

©2024 Walgreen Co.

†Our pharmacists recommend the Walgreens brand. We invite you to compare to national brands.

††This product is not manufactured or distributed by Bayer HealthCare LLC, owner of the registered trademark A+D®.

NDC 0363-5362-07

PACKAGE LABEL

Walgreens

Walgreens Pharmacist Recommended†

Compare to the active ingredients in A+D® First Aid Ointment††

First Aid A&D Ointment

LANOLIN 15.5%, PETROLATUM 53.4% / SKIN PROTECTANT

- Temporarily protects minor cuts, scrapes & burns
- Temporarily protects & helps prevent & relieve chapped, chafed or cracked skin
- NET WT 4 OZ (113 g)